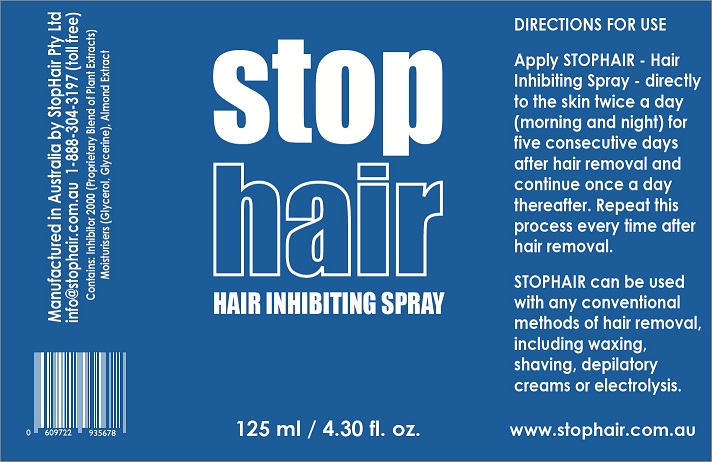 DRUG LABEL: stop hair
NDC: 50965-123 | Form: SPRAY
Manufacturer: STOP HAIR PTY LTD
Category: otc | Type: HUMAN OTC DRUG LABEL
Date: 20120616

ACTIVE INGREDIENTS: Citric Acid Monohydrate 0.7 mg/100 mL
INACTIVE INGREDIENTS: GLYCERIN; WATER; ALMOND

Active Ingredient

ACTIVE INGREDIENT

Citric Acid Monohydrate 0.7 % w/v

Purpose

DEPILATORY/HAIR INHIBITOR

Keep Out of Reach of Children.

Indication and Usage

DEPILATORY/HAIR INHIBITOR

Dosage and Administration

Step 1 Remove Hair:

The first is step isof the process is to remove the hair. Any method of hair removal can be used, such as shaving, waxing, etc., but as stated above, methods that remove the hair completely from the follicle are more effective.

Step 2: Apply STOPHAIR - Hair Inhibiting Spray

The second step of the process is to apply the STOPHAIR - Hair Inhibiting Spray. Lightly spray the STOPHAIR solution on the area the hair was removed from and massage in.

This process is to be repeated twice a day for five days after the hair was removed.

Step 3: Continue Applying STOPHAIR - Inhibiting Spray once a day

The third step of the process is to continue applying the STOPHAIR - Hair Inhibiting Spray once a day to the area the hair was removed from. As in Step 2, simply spray the STOPHAIR solution on the area the hair was removed from and lightly massage in.

Continue this process until the next time the hair needs to be removed. This step will vary in legth of time depending on the individual.

Step4: Repeat Steps 2 and 3

The fourth step of the process is to repeat Steps 2 and 3 until the hair permanently stops growing. As above, the number of times this step will have to be repeated depends on the hair properties of the individual.

SPRAY LIGHTLY ONTO SKIN TWICE DAILY FOR 5 DAYS.

Inactive Ingredient

Water, Almond Extract and Glycerine

WARNINGS

For external use only.